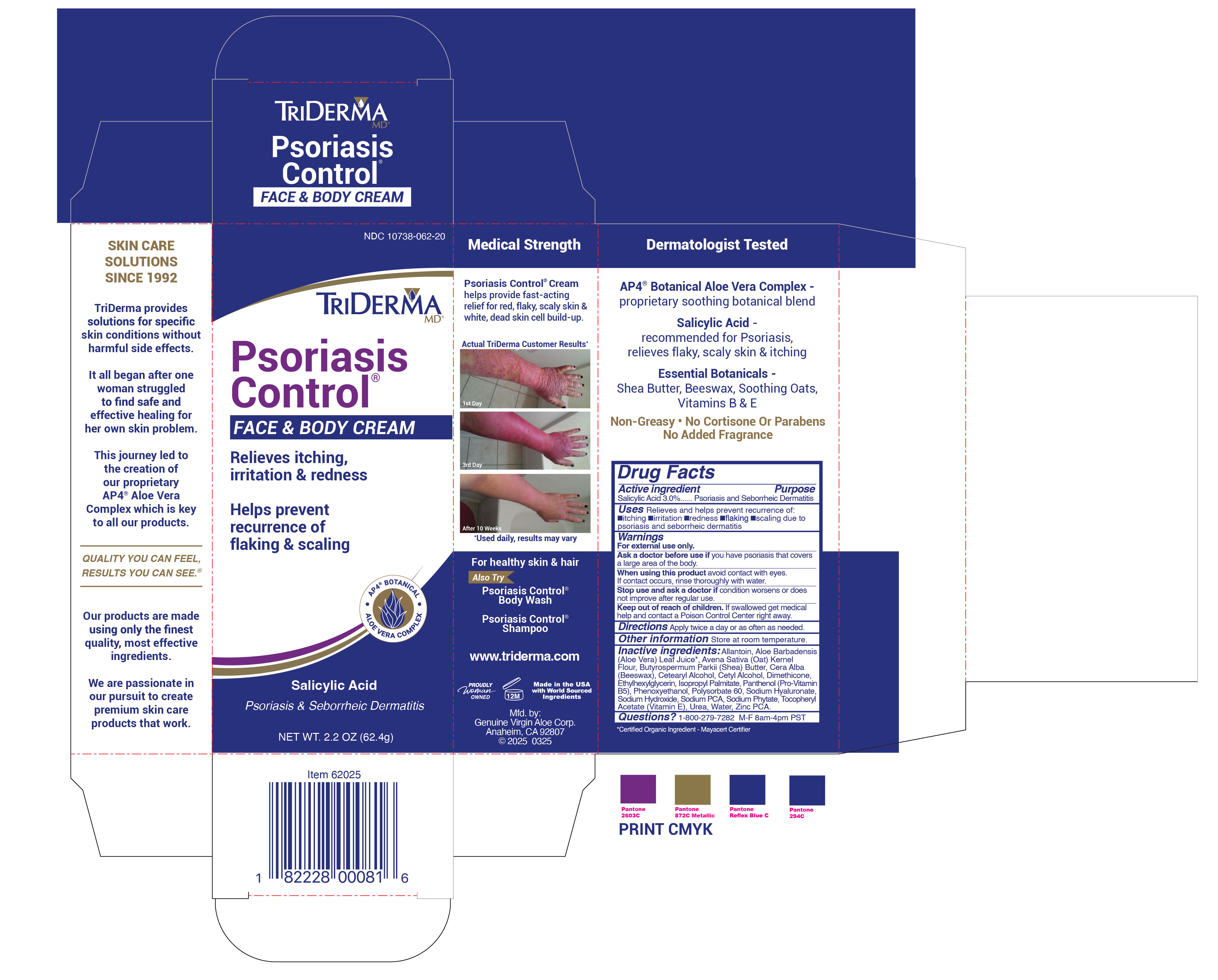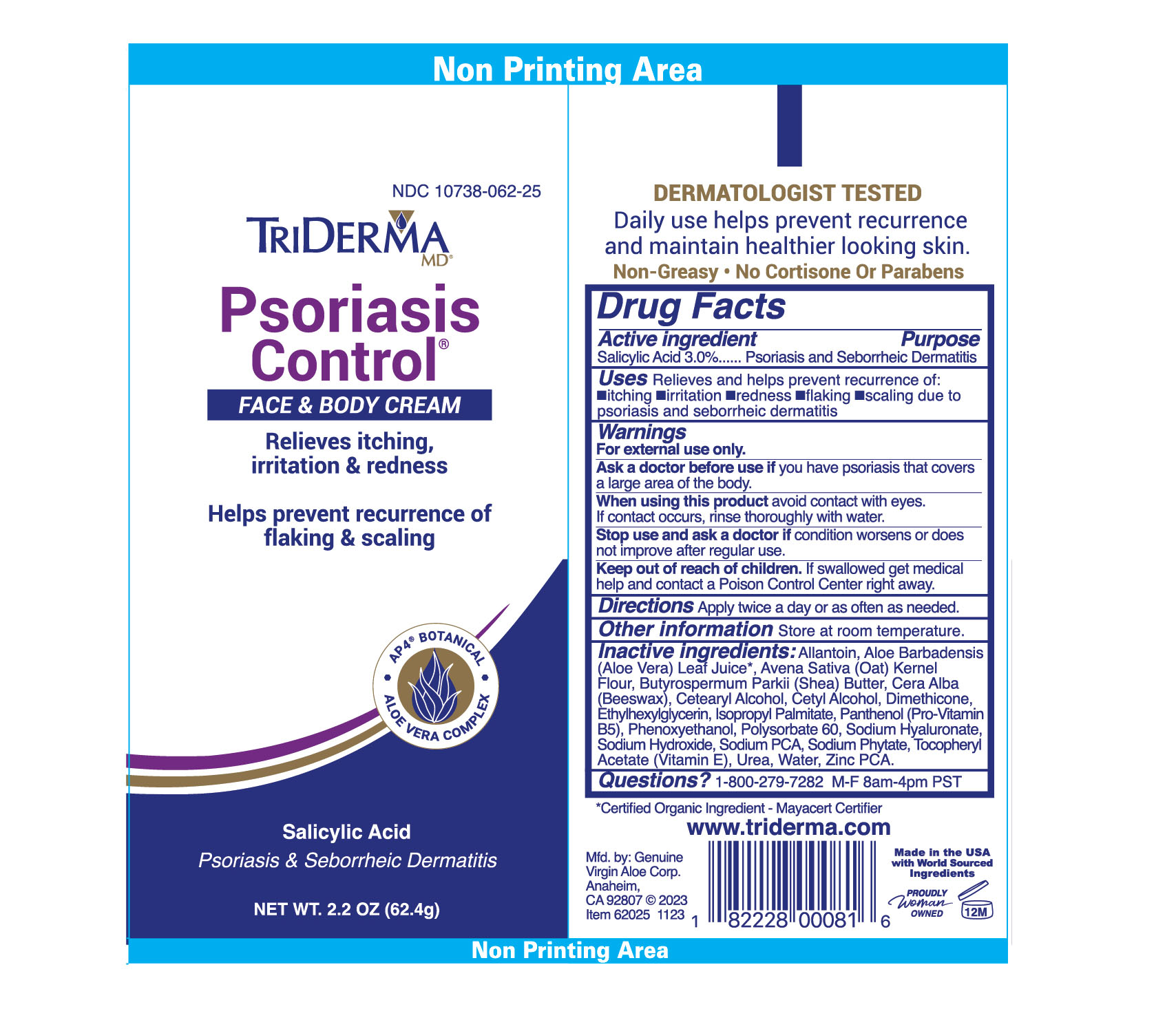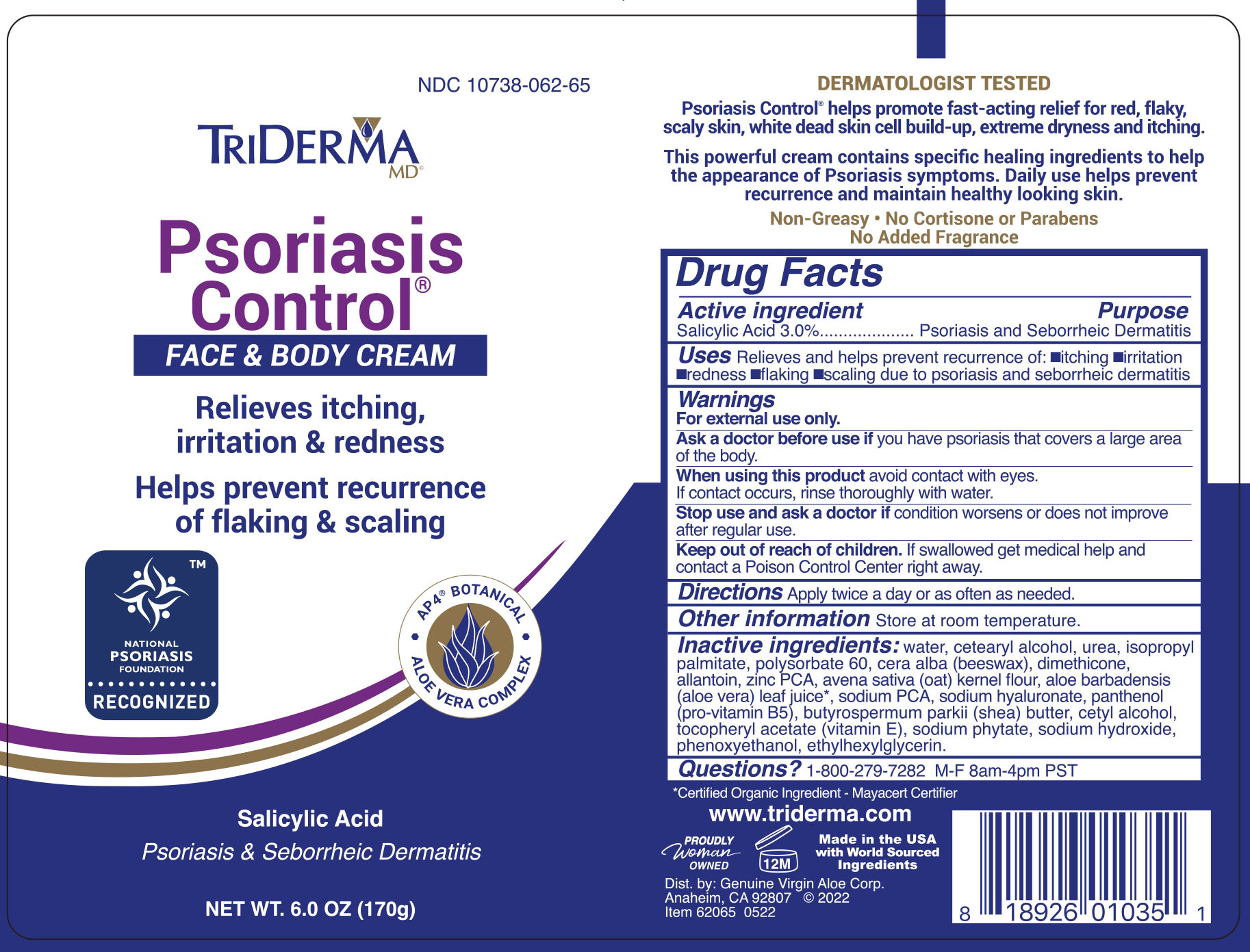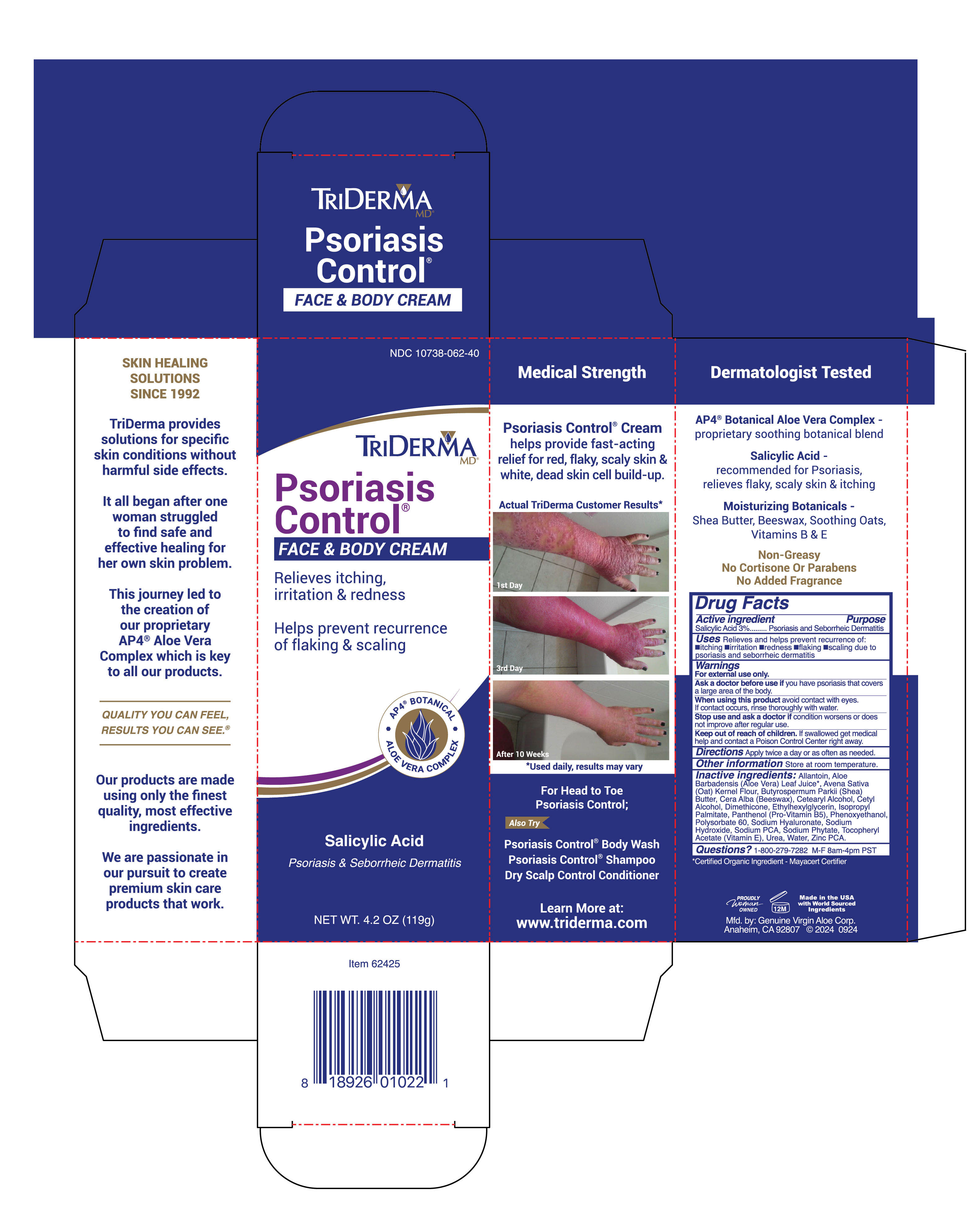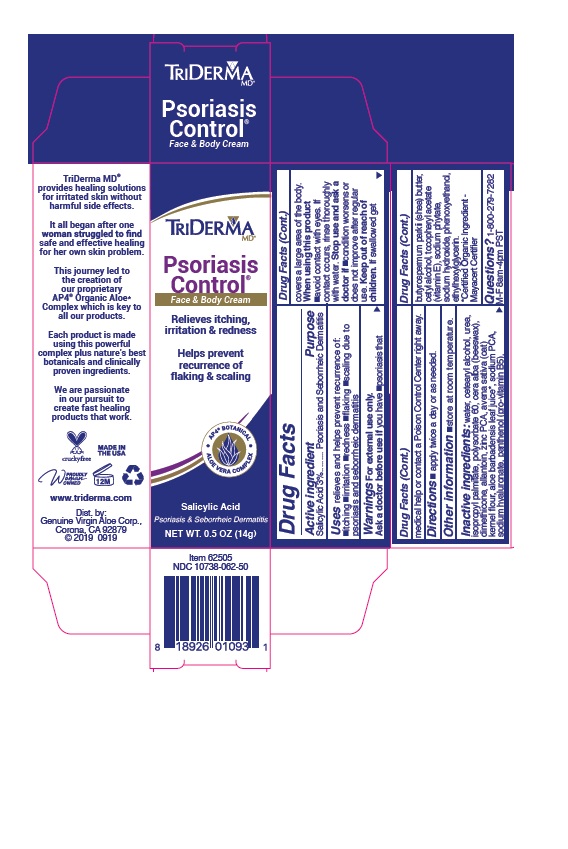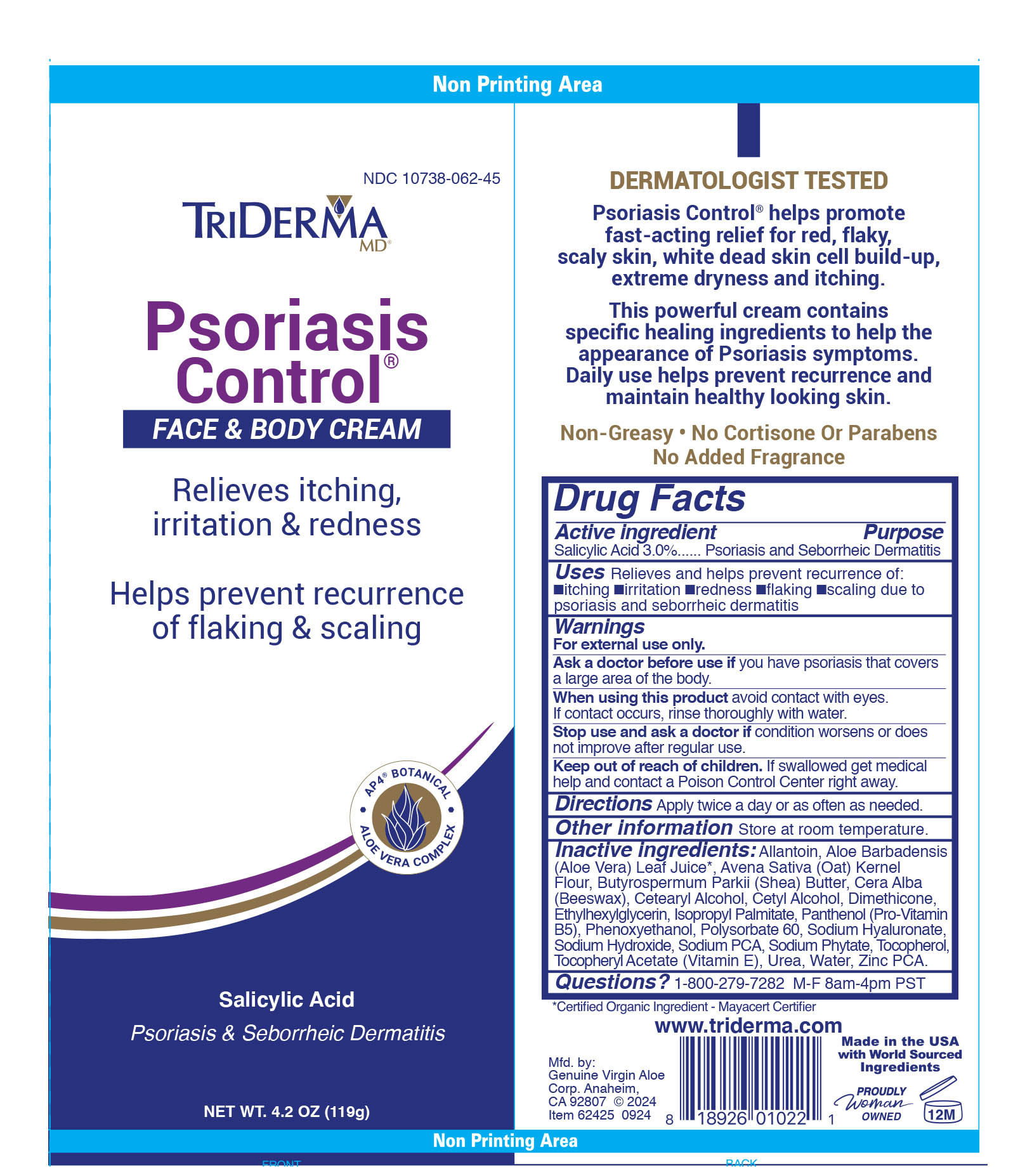 DRUG LABEL: TriDerma Psoriasis Control Face and Body Cream
NDC: 10738-062 | Form: CREAM
Manufacturer: Genuine Virgin Aloe Corporation
Category: otc | Type: HUMAN OTC DRUG LABEL
Date: 20260127

ACTIVE INGREDIENTS: SALICYLIC ACID 3 g/100 g
INACTIVE INGREDIENTS: WATER; CETOSTEARYL ALCOHOL; UREA; ISOPROPYL PALMITATE; POLYSORBATE 60; WHITE WAX; DIMETHICONE; ALLANTOIN; ZINC PIDOLATE; ALOE VERA LEAF; SODIUM PYRROLIDONE CARBOXYLATE; OAT BRAN; HYALURONATE SODIUM; PANTHENOL; SHEA BUTTER; CETYL ALCOHOL; .ALPHA.-TOCOPHEROL ACETATE; PHYTATE SODIUM; SODIUM HYDROXIDE; PHENOXYETHANOL; ETHYLHEXYLGLYCERIN

TriDerma Psoriasis Control Face & Body Cream

Active ingredient

Salicylic Acid 3%

Purpose

Psoriasis and Seborrheic Dermatitis

INDICATIONS AND USAGE

Uses relieves and helps prevent recurrence of: •itching •irritation •redness •flaking •scaling due to psoriasis and seborrheic dermatitis

Warnings For external use only.

Ask a doctor before use if you have •psoriasis that covers a large area of the body.

When using this product •avoid contact with eyes. If contact occurs, rinse thoroughly with water.

Stop use and ask a doctor if •condition worsens or does not improve after regular use.

Keep out of reach of children. If swallowed get medical help or contact a Poison Control Center right away.

DOSAGE AND ADMINISTRATION

Directions • apply twice a day or as needed.

Other information •store at room temperature.

Inactive ingredients:
allantoin, aloe barbadensis leaf juice*, avena sativa (oat) kernel flour, butyrospermum parkii (shea) butter, cera alba (beeswax), cetearyl alcohol, cetyl alcohol, dimethicone, ethylhexylglycerin, isopropyl palmitate, panthenol (pro-vitamin B5), phenoxyethanol, polysorbate 60, sodium hyaluronate, sodium hydroxide, sodium PCA, sodium phytate, tocopheryl acetate (vitamin E), urea, water, zinc PCA

*Certified Organic Ingredient - Mayacert Certifier

QUESTIONS

Questions? 1-800-279-7282 M-F 8am-4pm PST

Relieves itching, irritation & redness

Helps prevent recurrence of flaking & scaling

AP4® BOTANICAL • ALOE VERA COMPLEX

Maximum Strength

Healing Botanicals

Psoriasis Control® visibly reduces white, scaly skin, redness and dead skin cell build-up. It's specifically formulated with powerful healing botanicals and active ingredients to help relieve extreme dryness, itching and the look of Psoriasis symptoms.

Daily use helps prevent recurrence due to Psoriasis and Seborrheic Dermatitis.

Non-Greasy• No Cortisone Or Parabens No Added Fragrance

Dermatologist Tested

AP4® Organic Aloe* Complex-a proprietary blend

Salicylic Acid - recommended for Psoriasis, relieves flaky, scaly skin & itching

Avena Sativa Oat, Shea Butter & Beeswax

Vitamins B & E

EXPERTS IN SKIN HEALING SINCE 1992

TriDerma MD® provides healing solutions for irritated skin without harmful side effects.

It all began after one woman struggled to find safe and effective healing for her own skin problem.

This journey led to the creation of our proprietary AP4® Organic Aloe* Complex which is key to all our products.

QUALITY YOU CAN FEEL, RESULTS YOU CAN SEE®.

Each product is made using this powerful complex plus nature’s best botanicals and clinically proven ingredients.

We are passionate in our pursuit to create fast healing products that work.

www.triderma.com

Mfd. by:
Genuine Virgin Aloe Corp.,
Anaheim, CA 92807

Packaging

Triderma Psoriasis Control Cream

Relieves itching, irritation & redness

Helps prevent recurrence of flaking & scaling

AP4 ® BOTANICAL • ALOE VERA COMPLEX

Maximum Strength

Healing Botanicals

Psoriasis Control ® visibly reduces white, scaly skin, redness and dead skin cell build-up. It's specifically formulated with powerful healing botanicals and active ingredients to help relieve extreme dryness, itching and the look of Psoriasis symptoms.

Daily use helps prevent recurrence due to Psoriasis and Seborrheic Dermatitis.

Non-Greasy • No Cortisone Or Parabens No Added Fragrance

Dermatologist Tested

AP4® Organic Aloe* Complex-a proprietary blend

Salicylic Acid - recommended for Psoriasis, relieves flaky, scaly skin & itching

Avena Sativa Oat, Shea Butter & Beeswax

Vitamins B & E

EXPERTS IN SKIN HEALING SINCE 1992

TriDerma MD ® provides healing solutions for irritated skin without harmful side effects.

It all began after one woman struggled to find safe and effective healing for her own skin problem.

This journey led to the creation of our proprietary AP4 ® Organic Aloe* Complex which is key to all our products.

QUALITY YOU CAN FEEL, RESULTS YOU CAN SEE ®.

Each product is made using this powerful complex plus nature’s best botanicals and clinically proven ingredients.

We are passionate in our pursuit to create fast healing products that work.